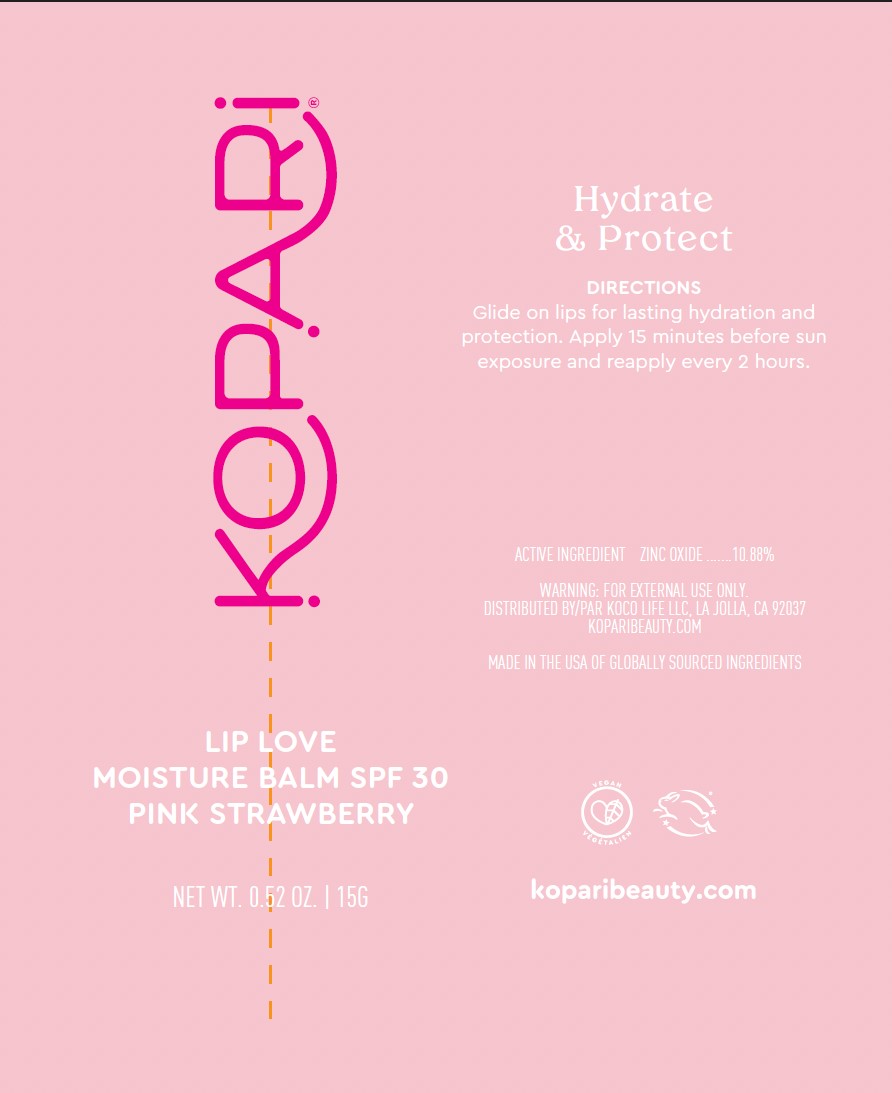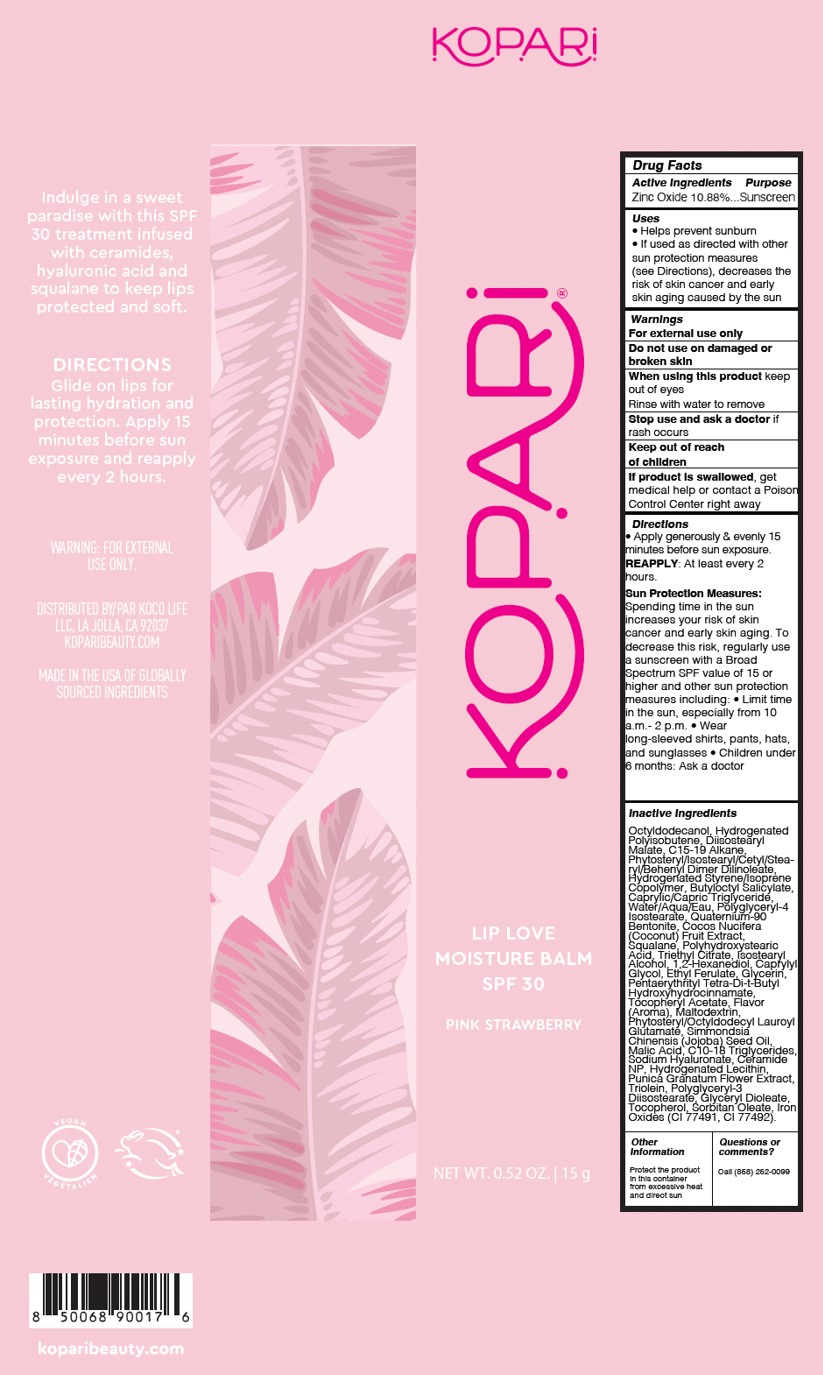 DRUG LABEL: Lip Love Moisture Balm SPF30 - Pink Strawberry
NDC: 84130-014 | Form: GEL
Manufacturer: Koco Life LLC
Category: otc | Type: HUMAN OTC DRUG LABEL
Date: 20250506

ACTIVE INGREDIENTS: ZINC OXIDE 10.88 g/100 g
INACTIVE INGREDIENTS: COCOS NUCIFERA (COCONUT) FRUIT; CAPRYLYL GLYCOL; OCTYLDODECANOL; CI 77492; DIISOSTEARYL MALATE; ETHYL FERULATE; HYDROGENATED SOYBEAN LECITHIN; GLYCERYL DIOLEATE; POLYGLYCERYL-4 ISOSTEARATE; PUNICA GRANATUM FLOWER; BUTYLOCTYL SALICYLATE; WATER; .ALPHA.-TOCOPHEROL ACETATE; JOJOBA OIL; CI 77491; 1,2-HEXANEDIOL; SQUALANE; POLYGLYCERYL-3 DIISOSTEARATE; C15-19 ALKANE; MALTODEXTRIN; MALIC ACID; TOCOPHEROL; C10-18 TRIGLYCERIDES; CERAMIDE NP; SORBITAN OLEATE; HYDROGENATED POLYISOBUTENE 8; TRIOLEIN; QUATERNIUM-90 BENTONITE; POLYHYDROXYSTEARIC ACID (2300 MW); TRIETHYL CITRATE; ISOSTEARYL ALCOHOL; GLYCERIN; SODIUM HYALURONATE; PHYTOSTERYL/ISOSTEARYL/CETYL/STEARYL/BEHENYL DIMER DILINOLEATE; CAPRYLIC/CAPRIC TRIGLYCERIDE; PENTAERYTHRITYL TETRA-DI-T-BUTYL HYDROXYHYDROCINNAMATE; PHYTOSTERYL/OCTYLDODECYL LAUROYL GLUTAMATE

Lip Love Moisture Balm SPF30 - Pink Strawberry

Active ingredients

Zinc Oxide 10.88%

Purpose

Zinc Oxide 10.88%...Sunscreen

Uses

• Helps prevent sunburn

• If used as directed with othersun protection measures(see Directions), decreases therisk of skin cancer and earlyskin aging caused by the sun

Warnings

For external use only

Do not use on damaged or broken skin

When using this product keep out of eyes

Rinse with water to remove

Stop use and ask a doctor if rash occurs

Stop use and ask a doctor if rash occurs

Keep out of reach of children
If product is swallowed, get medical help or contact a Poison Control Center right away

Directions

• Apply generously & evenly 15 minutes before sun exposure. REAPPLY: At least every 2 hours.

Sun Protection Measures: Spending time in the sun increases your risk of skin cancer and early skin aging. To decrease this risk, regularly use a sunscreen with a Broad Spectrum SPF value of 15 or higher and other sun protection measures including: • Limit time in the sun, especially from 10 a.m.- 2 p.m. • Wearlong-sleeved shirts, pants, hats, and sunglasses • Children under 6 months: Ask a doctor

Inactive Ingredients

Octyldodecanol, Hydrogenated Polyisobutene, Diisostearyl Malate, C15-19 Alkane, Phytosteryl/Isostearyl/Cetyl/Stearyl/Behenyl Dimer Dilinoleate, Hydrogenated Styrene/Isoprene Copolymer, Butyloctyl Salicylate, Caprylic/Capric Triglyceride, Water/Aqua/Eau, Polyglyceryl-4 Isostearate, Quaternium-90 Bentonite, Cocos Nucifera (Coconut) Fruit Extract, Squalane, Polyhydroxystearic Acid, Triethyl Citrate, Isostearyl Alcohol, 1,2-Hexanediol, Caprylyl Glycol, Ethyl Ferulate, Glycerin, Pentaerythrityl Tetra-Di-t-Butyl Hydroxyhydrocinnamate, Tocopheryl Acetate, Flavor (Aroma), Maltodextrin, Phytosteryl/Octyldodecyl Lauroyl Glutamate, Simmondsia Chinensis (Jojoba) Seed Oil, Malic Acid, C10-18 Triglycerides, Sodium Hyaluronate, Ceramide NP, Hydrogenated Lecithin, Punica Granatum Flower Extract, Triolein, Polyglyceryl-3 Diisostearate, Glyceryl Dioleate, Tocopherol, Sorbitan Oleate, Iron Oxides (CI 77491, CI 77492)

Other information

Protect the product in this container from excessive heat and direct sun

Questions or comments?

Call (858) 252-0099